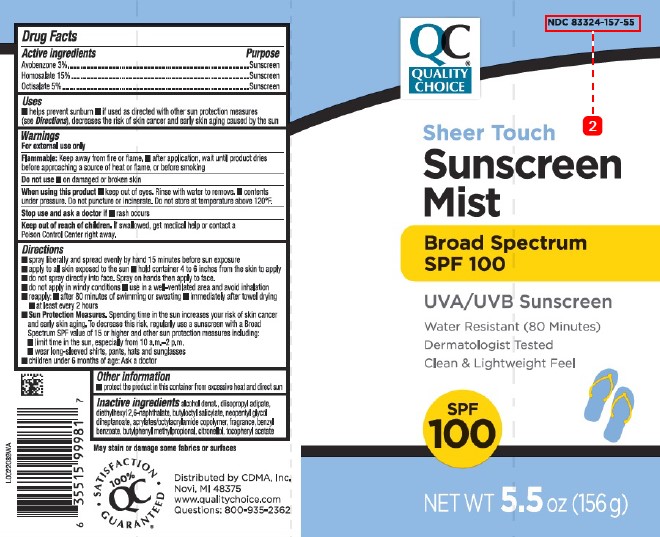 DRUG LABEL: Avobenzone, Homosalate, Octisalate
NDC: 83324-157 | Form: SPRAY
Manufacturer: Chain Drug Marketing Association
Category: otc | Type: HUMAN OTC DRUG LABEL
Date: 20260227

ACTIVE INGREDIENTS: AVOBENZONE 30 mg/1 g; HOMOSALATE 150 mg/1 g; OCTISALATE 50 mg/1 g
INACTIVE INGREDIENTS: ALCOHOL; DIISOPROPYL ADIPATE; DIETHYLHEXYL 2,6-NAPHTHALATE; BUTYLOCTYL SALICYLATE; NEOPENTYL GLYCOL DIHEPTANOATE; ACRYLATE/ISOBUTYL METHACRYLATE/N-TERT-OCTYLACRYLAMIDE COPOLYMER (75000 MW); BENZYL BENZOATE; BUTYLPHENYL METHYLPROPIONAL; .BETA.-CITRONELLOL, (R)-; .ALPHA.-TOCOPHEROL ACETATE

Quality Choice D36.000/D36AA
Sheer Touch Sunscreen Mist SPF 100

Active ingredients

Avobenzone 3%

Homosalate 15%

Octisalate 5%

Purpose

Sunscreen

Uses

- helps prevent sunburn
- if used as directed with other sun protection measures (see Directions), decreases the risk of skin cancer and early skin aging caused by the sun

Warnings

For external use only

Flammable: Keep away from fire or flame.

- after application, wait until product dries before approaching a source of heat or flame, or before smoking

Do not use

- on damaged or broken skin

When using this product

- keep out of eyes. Rinse with water to remove.
- contents under pressure. Do not puncture or incinerate. Do not store at temperature above 120ºF.

Stop use and ask a doctor if

- rash occurs

Keep out of reach of children.

If swallowed, get medical help or contact a Poison Control Center right away.

Directions

- spray liberally and spread evenly by hand 15 minutes before sun exposure
- apply to all skin exposed to the sun
- hold container 4 to 6 inches from the skin to apply
- do not spray directly into face. Spray on hands then apply to face.
- do not apply in windy conditions
- use in a well-ventilated area and avoid inhalation
- reapply:
- after 80 minutes of swimming or sweating
- immediately after towel drying
- at least every 2 hours
- Sun Protection Measures. Spending time in the sun increases your risk of skin cancer and early skin aging. To decrease this risk, regularly use a sunscreen with a Broad Spectrum SPF value of 15 or higher and other sun protection measures including:
- limit time in the sun, especially from 10 a.m.–2 p.m.
- wear long-sleeved shirts, pants, hats and sunglasses
- children under 6 months of age: Ask a doctor

Other information

- protect the product in this container from excessive heat and direct sun

Inactive ingredients

alcohol denat., diisopropyl adipate, diethylhexyl 2,6-naphthalate, butyloctyl salicylate, neopentyl glycol diheptanoate, acrylates/octylacrylamide copolymer, fragrance, benzyl benzoate, butylphenyl methylpropional, citronellol, tocopheryl acetate

ADVERSE REACTION

May stain or damage some fabrics or surfaces

100% QC SATISFACTION GUARANTEED

Distributed by CDMA, Inc.

Novi, MI 48375

www.qualitychoice.com

Questions: 800-935-2362

PRINCIPAL DISPLAY PANEL

NDC 83324-157-55

QC®

QUALITY CHOICE

Sheer Touch

Sunscreen

Mist

Broad Spectrum

SPF 100

UVA/UVB Sunscreen

Water Resistant (80 Minutes)

Dermatologist Tested

Clean & Lightweight Feel

SPF 100

NET WT 5.5 oz (156g)